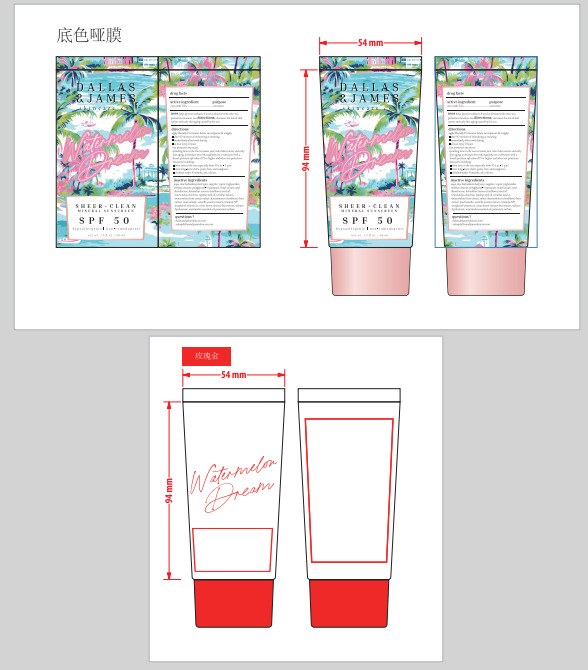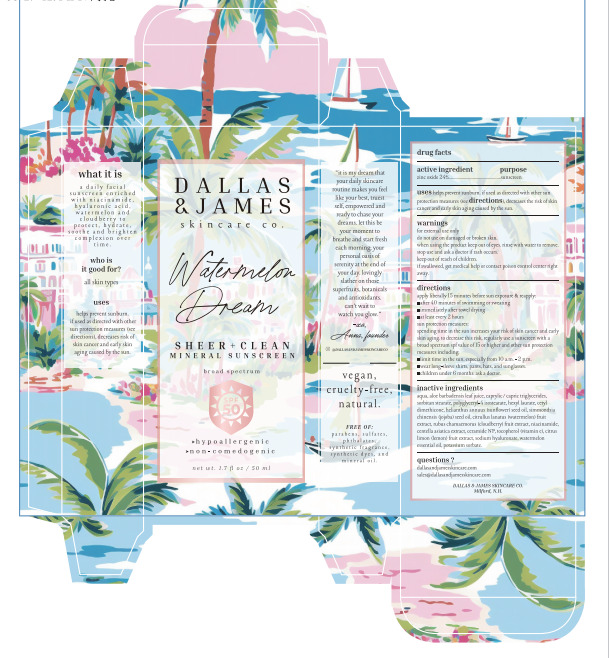 DRUG LABEL: DALLAS JAMES SKINCARE CO. SPF 50 Sunscreen
NDC: 83447-010 | Form: CREAM
Manufacturer: Guangzhou Fantesy Biotechnology Co.,Ltd
Category: otc | Type: HUMAN OTC DRUG LABEL
Date: 20260105

ACTIVE INGREDIENTS: ZINC OXIDE 24 g/100 mL
INACTIVE INGREDIENTS: CENTELLA ASIATICA TRITERPENOIDS; COCONUT OIL; POLYGLYCERYL-4 ISOSTEARATE; LEMON; CETYL DIMETHICONE 25; TOCOPHEROL; HYALURONATE SODIUM; POTASSIUM SORBATE; WATER; ALOE VERA LEAF; MEDIUM-CHAIN TRIGLYCERIDES; SORBITAN MONOSTEARATE; HEXYL LAURATE; CERAMIDE NS; JOJOBA OIL; WATERMELON; NIACINAMIDE

83447-010

ACTIVE INGREDIENT

Zinc Oxide 24%

PURPOSE

sunscreen

Uses

uses helps prevent sunburn. if used as directed with other sun protection measures (see directions), decreases the risk of skin
cancer and early skin aging caused by the sun.

Warnings

① For external use only.

② When using this product keep out of eyes.

Do not use on damaged or broken skin.

Keep out of reach of children. If product is swallowed, get medical help or contact a Poison Control Center right away.

Directions

apply liberally 15 minutes before sun exposure & reapply:
■after 40 minutes of swimming or sweating
■immediately after towel drying
■at least every 2 hours

Other information

sun protection measures: spending time in the sun increases your risk of skin cancer and early skin aging. to decrease

this risk, regularly use a sunscreen with a broad spectrum spf value of 15 or higher and other sun protection measures including:

■ limit time in the sun, especially from 10 a.m.-2 p.m.
■ wear long-sleeve shirts, pants, hats, and sunglasses.
■children under 6 n mornths: ask a doctor.

Inactive Ingredients

aqua, aloe barbadensis leaf juice, caprylic/ capric triglycerides, sorbitan stearate, polyglyceryl-4 isostearate, hexyl laurate, cetyl
dimethicone, helianthus annuus (sunflower) seed oil, simmondsia chinensis (jojoba) seed oil, citrullus lanatus
(watermelon) fruit extract, rubus chamaemorus (cloudberry) fruit extract, niacinamide, centella asiatica extract, ceramide NP,
tocopherol (vitamin e), citrus limon (lemon) fruit extract, sodium hyaluronate, watermelon essential oil, potassium sorbate.